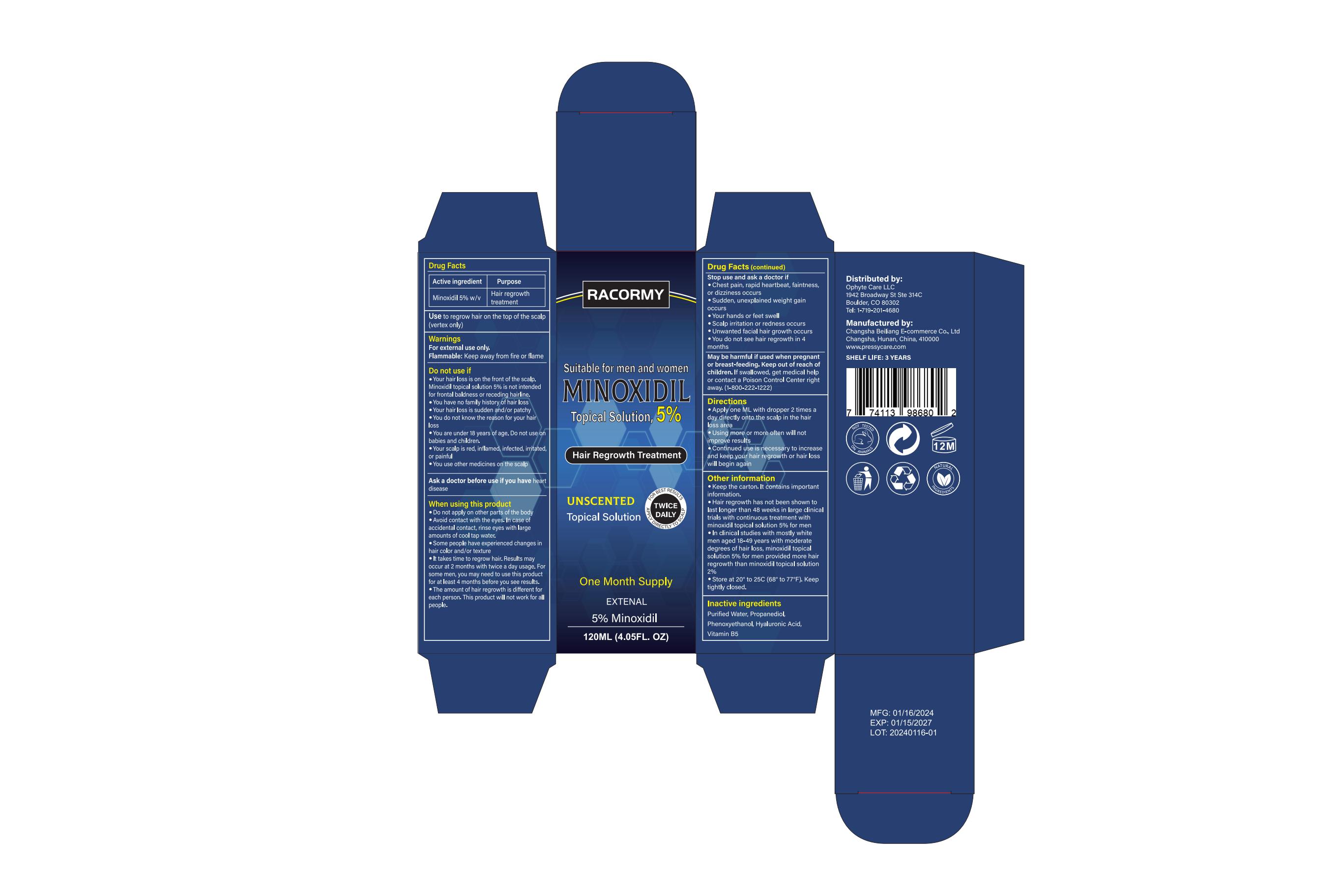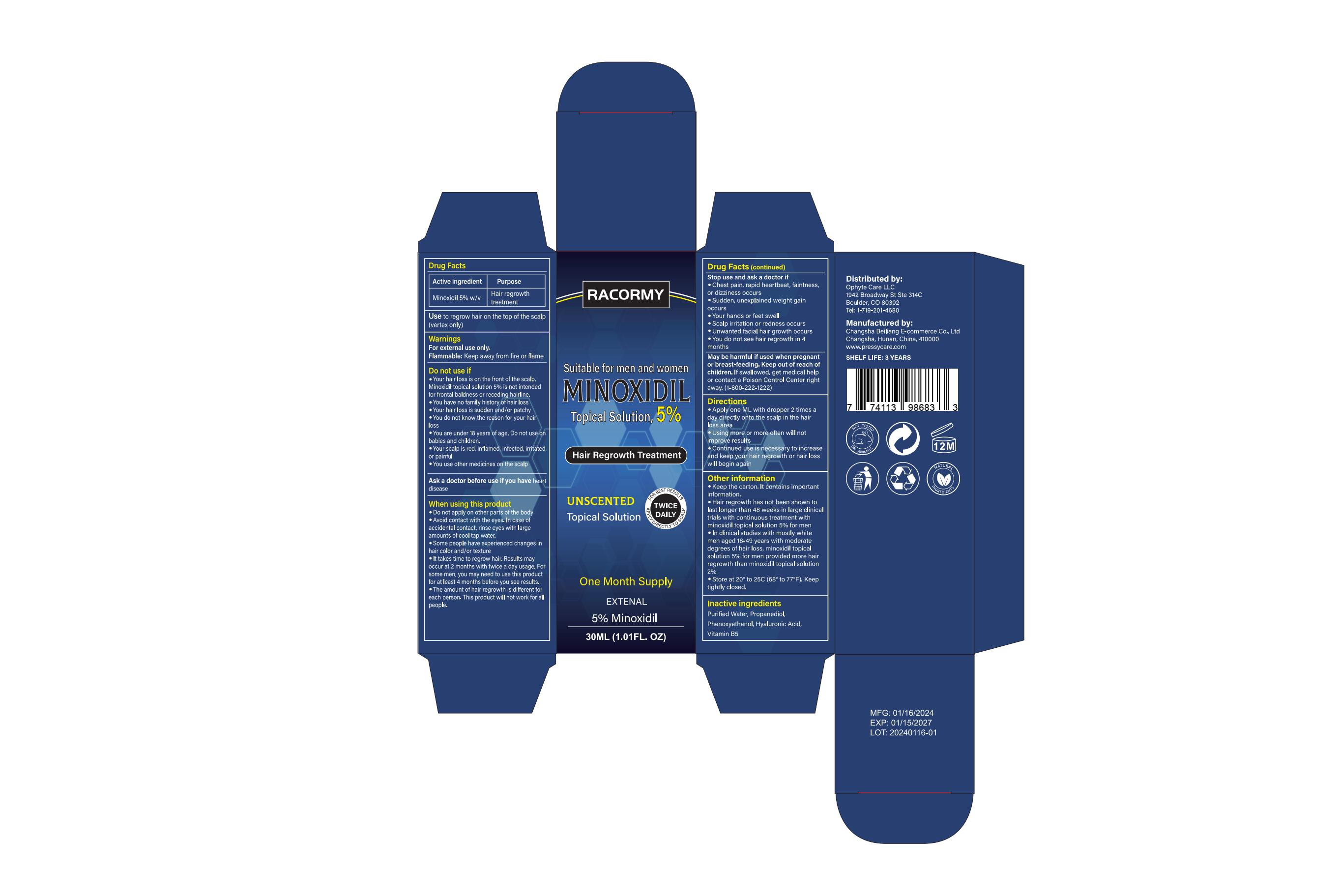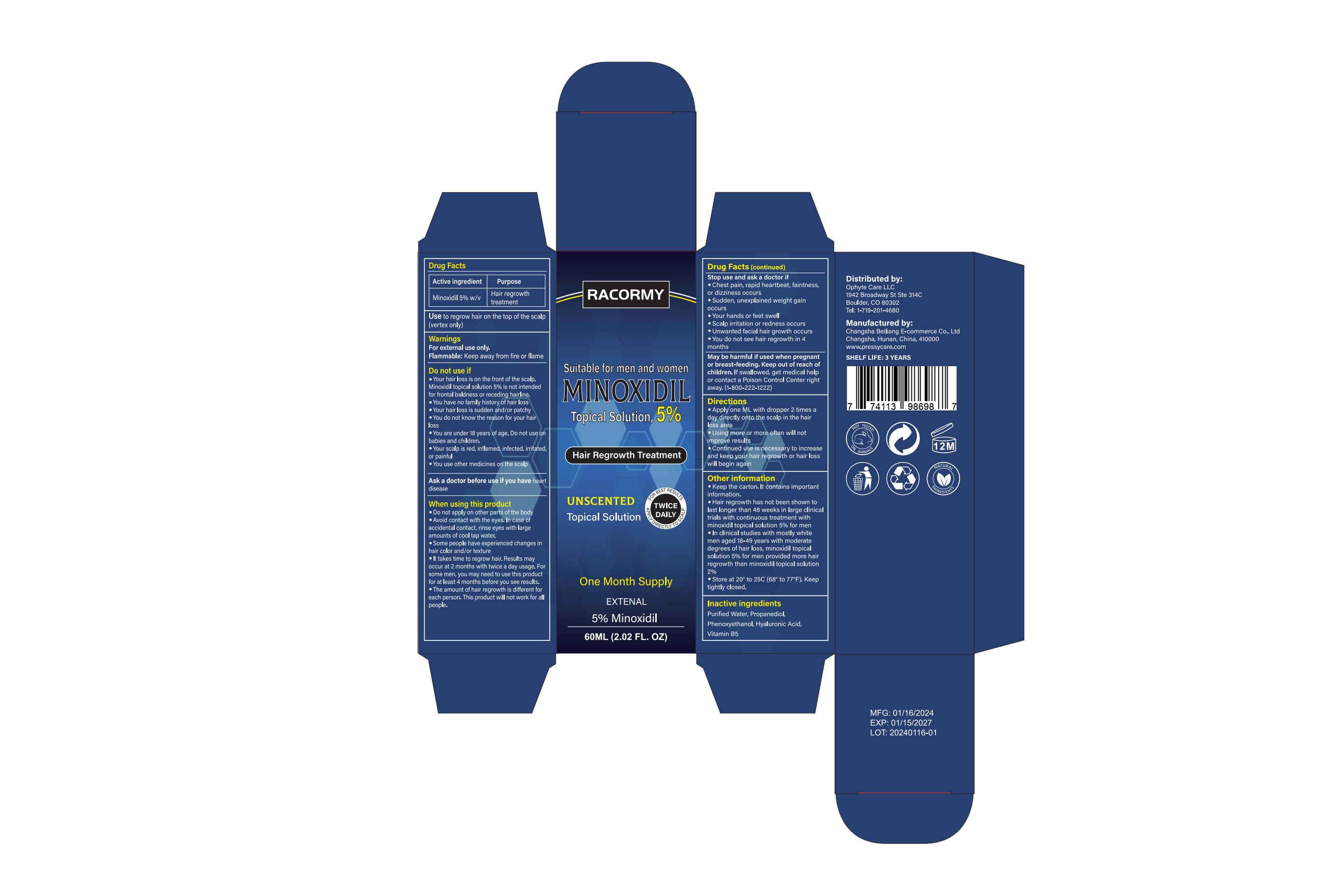 DRUG LABEL: RACORMY 5% Minoxidil Hair Growth Serum
NDC: 83887-003 | Form: LIQUID
Manufacturer: Changsha Beiliang E-commerce Co., Ltd
Category: otc | Type: HUMAN OTC DRUG LABEL
Date: 20240108

ACTIVE INGREDIENTS: MINOXIDIL 5 g/100 mL
INACTIVE INGREDIENTS: PROPANEDIOL; PHENOXYETHANOL; HYALURONIC ACID; PANTOTHENIC ACID; WATER

83887-003

Active Ingredient

Minoxidil 5%

Purpose

Hair regrowth treatment

Use

1.Do not apply on other parts of the body.
2.Avoid contact with the eyes. In case of accidental contact, rinse eyes with large amounts of cool tap water.
3.Some people have experienced changes in hair color and/or texture.
4.It takes time to regrow hair. Results may occur at 2 months with twice-a-day usage. For some men, you may need to use this product for at least 4 months before you see results.
5.The amount of hair regrowth is different for each person. This product will not work for all people.

Warnings

For external use only.
Flammable: Keep away from fire or flame.

Do not use

1.Your hair loss is on the front of the scalp.
2.You have no family history of hair loss.
3. hair loss is sudden and/or patchy.
4.You do not know the reason for your hair loss.
5.You are under 18 years of age. Do not use on babies and children.
6.Your scalp is red, inflamed, infected, irritated, or painful.
7.You use other medicines on the scalp.

When Using

1.Do not apply on other parts of the body.
2.Avoid contact with the eyes. In case of accidental contact, rinse eyes with large amounts of cool tap water.
3.Some people have experienced changes in hair color and/or texture.
4.It takes time to regrow hair. Results may occur at 2 months with twice-a-day usage. For some men, you may need to use this product for at least 4 months before you see results.
5.The amount of hair regrowth is different for each person. This product will not work for all people.

Stop Use

1.Chest pain, rapid heartbeat, faintness, or dizziness occurs.
2.Sudden, unexplained weight gain occurs.
3.Your hands or feet swell.
4.Scalp irritation or redness occurs.
5.Unwanted facial hair growth occurs.
6.You do not see hair regrowth in 4 months.

Ask Doctor

May be harmful if used when pregnant or breast-feeding. Keep out of reach of children. If swallowed, get medical help or contact a Poison Control Center right away at 1-800-222-1222.

Keep Oot Of Reach Of Children

Directions

1.Apply one ML with a dropper two times a day directly onto the scalp in the hair loss area.
2.Using more or more often will not improve results.
3.Continued use is necessary to increase and maintain hair regrowth; otherwise, hair loss will likely resume.

Other information

1.Keep the carton. It contains important information.
Hair regrowth has not been shown to last longer than 48 weeks in large clinical trials with continuous treatment with minoxidil topical solution 5% for men.
2.In clinical studies with mostly white men aged 18-49 years with moderate degrees of hair loss, minoxidil topical solution 5% for men provided more hair regrowth than minoxidil topical solution 2%.
3.Store at 20°C to 25°C (68°F to 77°F). Keep tightly closed.

Inactive ingredients

Purified Water，Propanediol，Phenoxyethanol，Hyaluronic Acid，Vitamin B5